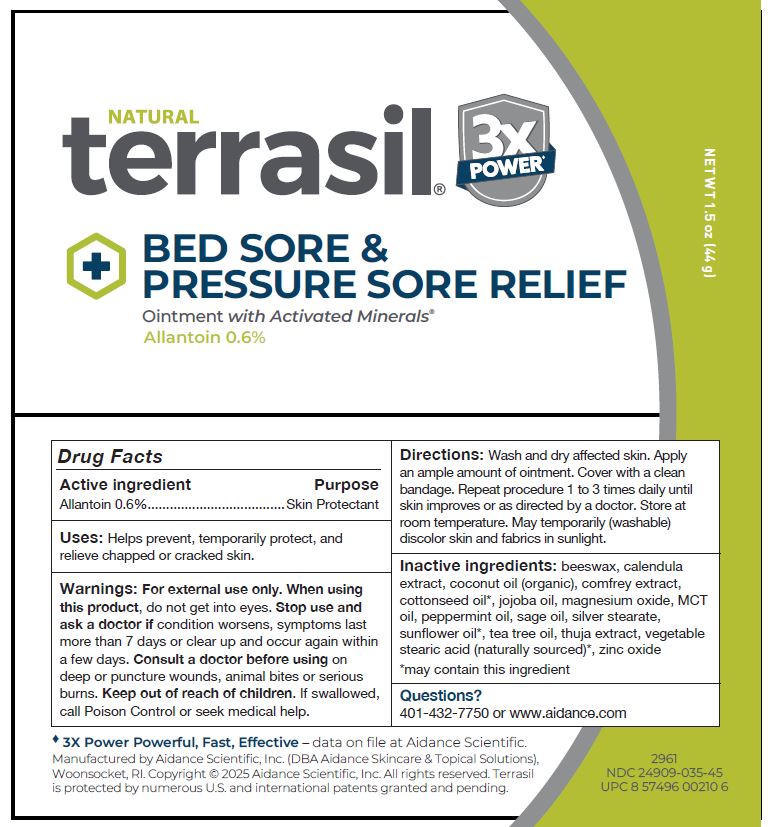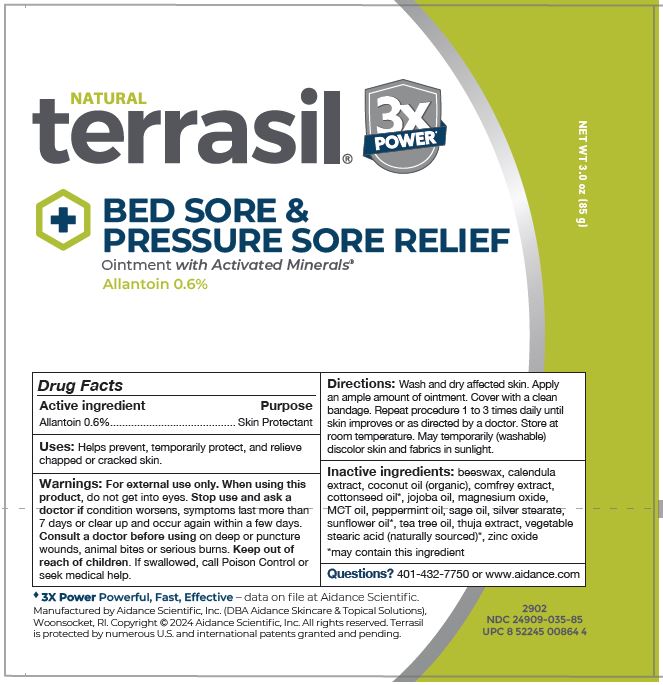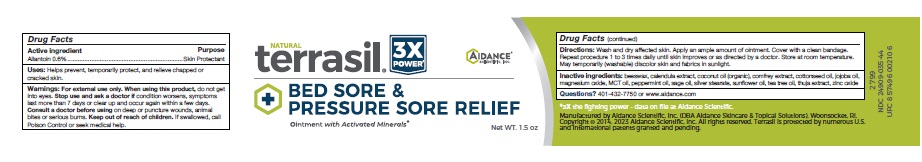 DRUG LABEL: terrasil Bed Sore and Pressure Sore Relief
NDC: 24909-035 | Form: OINTMENT
Manufacturer: Aidance Scientific, Inc, DBA Aidance Skincare & Topical Solutions
Category: otc | Type: HUMAN OTC DRUG LABEL
Date: 20251118

ACTIVE INGREDIENTS: ALLANTOIN 0.6 g/100 g
INACTIVE INGREDIENTS: YELLOW WAX; CALENDULA OFFICINALIS FLOWER; COCONUT OIL; COMFREY ROOT; COTTONSEED OIL; JOJOBA OIL; MAGNESIUM OXIDE; PALM OIL; PEPPERMINT OIL; SAGE OIL; SILVER STEARATE; SUNFLOWER OIL; TEA TREE OIL; THUJA OCCIDENTALIS LEAF; ZINC OXIDE

24909-035 terrasil Bed Sore & Pressure Sore

Active ingredient

Allantoin 0.6%

Purpose

Skin Protectant

Uses

Helps prevent, temporarily protect, and relieve chapped or cracked skin.

Warnings

For external use only. When using this product, do not get into eyes. Stop use and ask a doctor if condition worsens, symptoms last more than 7 days or clear up and occur again within a few days. Consult a doctor before using on deep or puncture wounds, animal bites or serious burns. Keep out of reach of children. If swallowed, call Poison Control or seek medical help.

Keep out of reach of children.

Directions

Wash and dry affected skin. Apply an ample amount of ointment. Cover with a clean bandage. Repeat procedure 1 to 3 times daily until skin improves or as directed by a doctor.

Inactive ingredients

beeswax, calendula extract, coconut oil (organic), comfrey extract, cottonseed oil, jojoba oil, magnesium oxide, MCT oil, peppermint oil, sage oil, silver stearate, sunflower oil, tea tree oil, thuja extract, zinc oxide

Other information

Store at room temperature. May temporarily (washable) discolor skin and fabrics in sunlight.